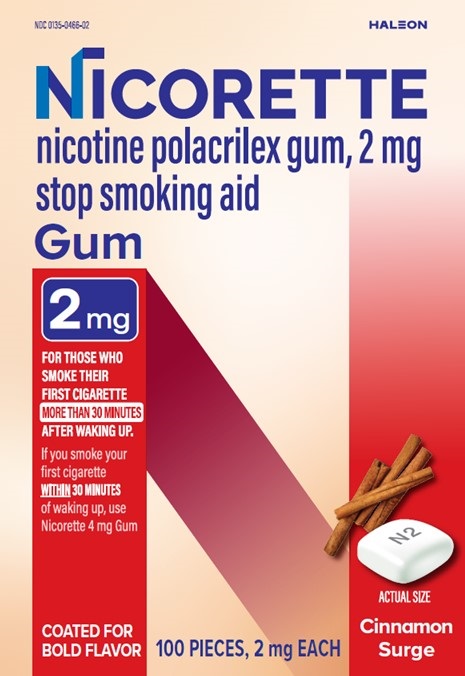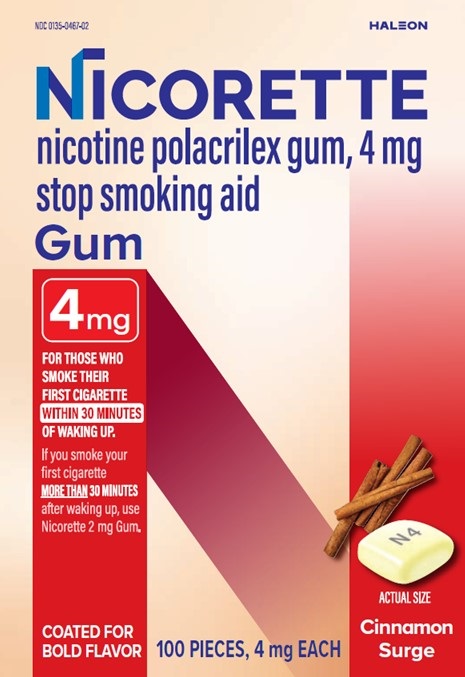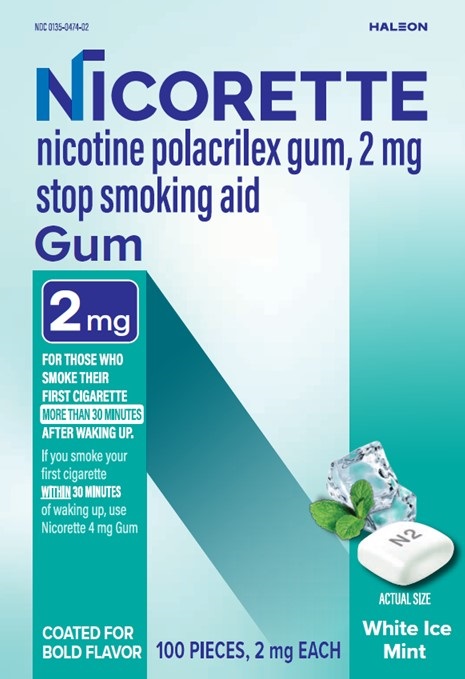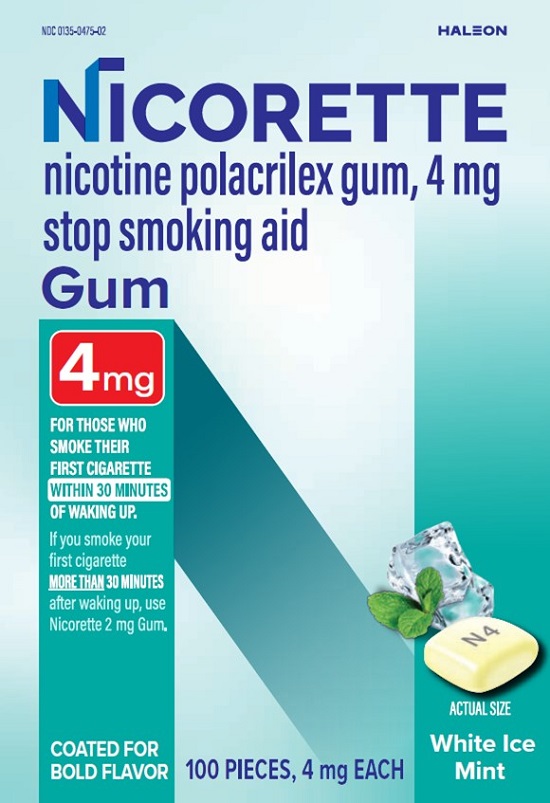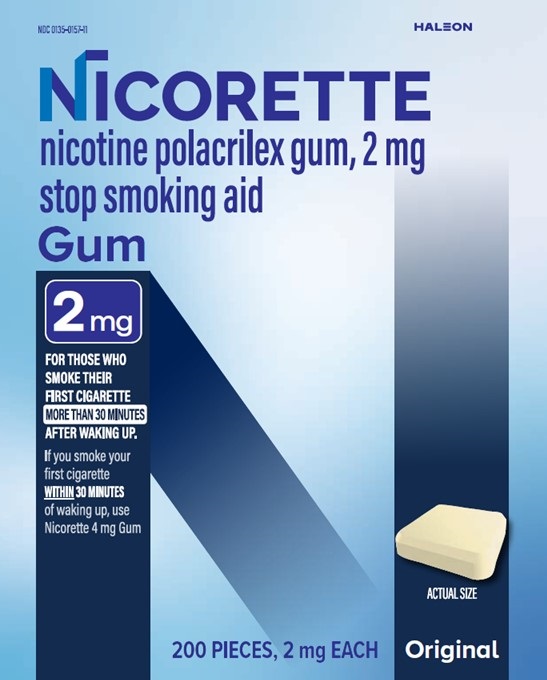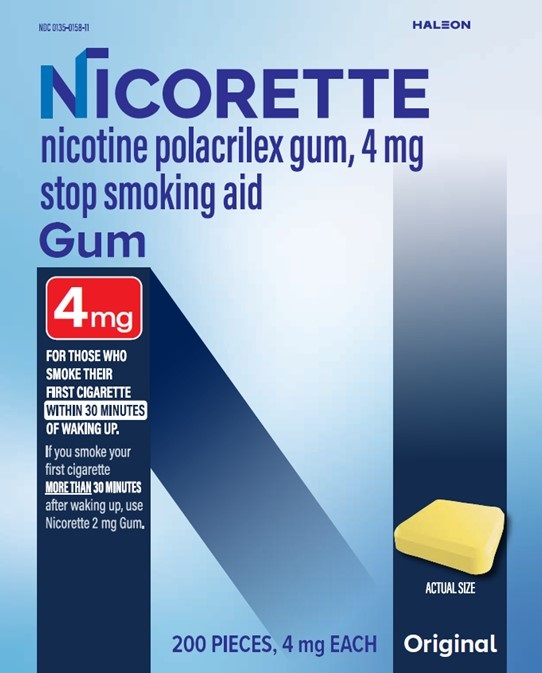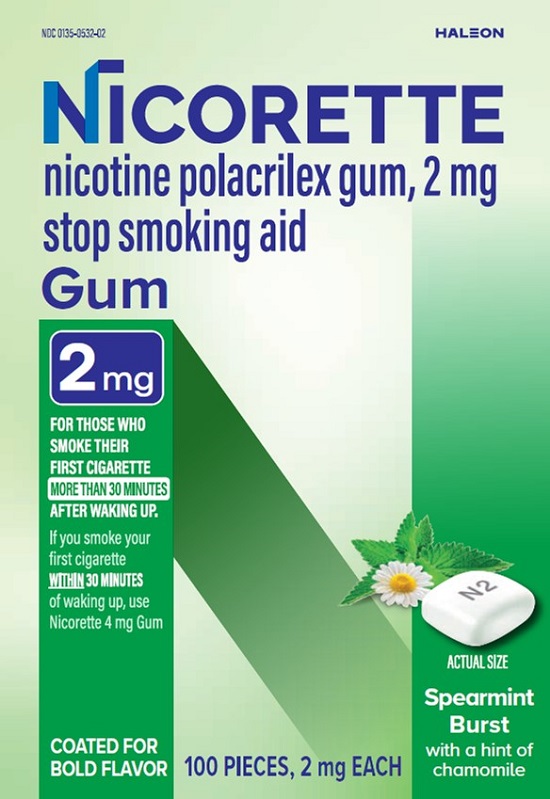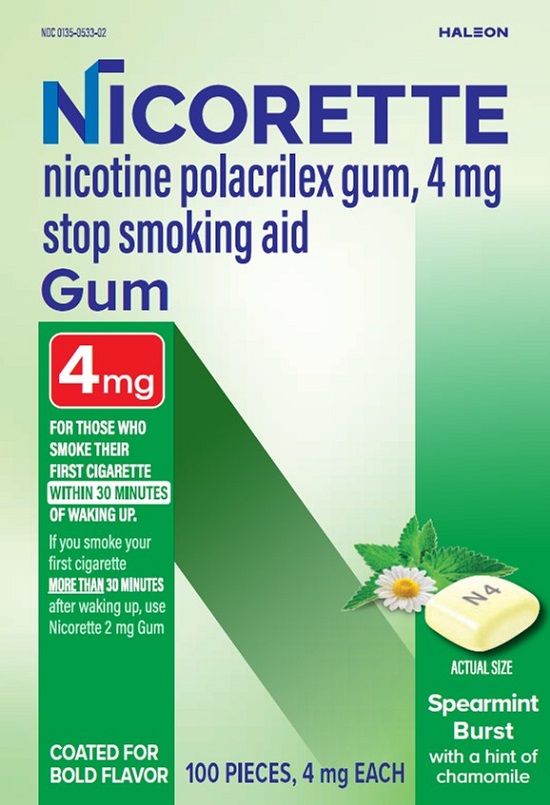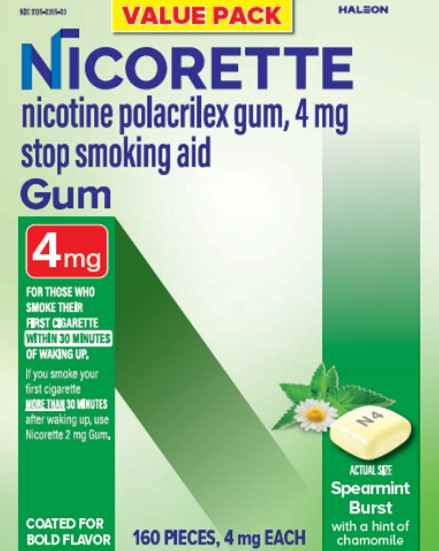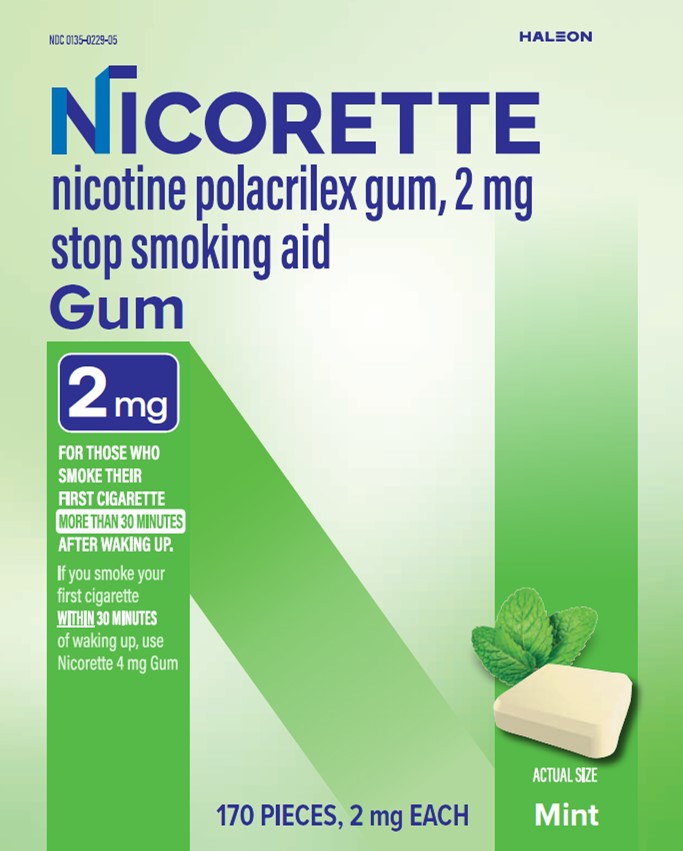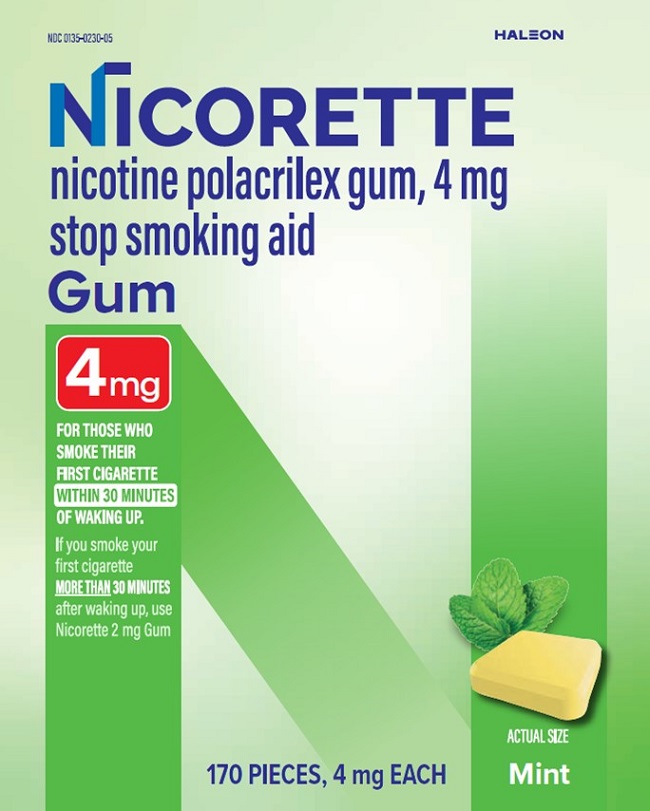 DRUG LABEL: Nicorette

NDC: 0135-0474 | Form: GUM, CHEWING
Manufacturer: Haleon US Holdings LLC
Category: otc | Type: HUMAN OTC DRUG LABEL
Date: 20240813

ACTIVE INGREDIENTS: NICOTINE 2 mg/1 1
INACTIVE INGREDIENTS: POLACRILIN; ACESULFAME POTASSIUM; CARNAUBA WAX; HYPROMELLOSE, UNSPECIFIED; MAGNESIUM OXIDE; MENTHOL, UNSPECIFIED FORM; PEPPERMINT OIL; POLYSORBATE 80; SODIUM BICARBONATE; SODIUM CARBONATE; SUCRALOSE; TITANIUM DIOXIDE; XYLITOL

Drug Facts

Active ingredient (in each chewing piece)

Nicotine polacrilex (equal to 2 mg nicotine)

Nicotine polacrilex (equal to 4 mg nicotine)

Purpose

Stop smoking aid

Use

- reduces withdrawal symptoms, including nicotine craving, associated with quitting smoking

Warnings

If you are pregnant or breast-feeding, only use this medicine on the advice of your health care provider.

Smoking can seriously harm your child. Try to stop smoking without using any nicotine replacement medicine. This medicine is believed to be safer than smoking. However, the risks to your child from this medicine are not fully known.

Ask a doctor before use if you have

- a sodium-restricted diet
- heart disease, recent heart attack, or irregular heartbeat. Nicotine can increase your heart rate.
- high blood pressure not controlled with medication. Nicotine can increase blood pressure.
- stomach ulcer or diabetes
- history of seizures

Ask a doctor or a pharmacist before use if you are

- using a non-nicotine stop smoking drug
- taking a prescription medicine for depression or asthma. Your prescription dose may need to be adjusted.

Stop use and ask a doctor if

- mouth, teeth or jaw problems occur
- irregular heartbeat or palpitations occur
- you get symptoms of nicotine overdose such as nausea, vomiting, dizziness, diarrhea, weakness and rapid heartbeat
- (For Cinnamon Surge)oral blistering occurs
- you have symptoms of an allergic reaction (such as difficulty breathing or rash)

Keep out of reach of children and pets.

Pieces of nicotine gum may have enough nicotine to make children and pets sick. Wrap used pieces of gum in paper and throw away in the trash. In case of overdose, get medical help or contact a Poison Control Center right away.

Directions (2 mg)

- if you are under 18 years of age, ask a doctor before use
- before using this product, read the enclosed User’s Guide for complete directions and other important information
- begin using the gum on your quit day
- if you smoke your first cigarette within 30 minutes of waking up,use 4 mg nicotine gum
- if you smoke your first cigarette more than 30 minutes after waking up,use 2 mg nicotine gum according to the following 12 week schedule:

Weeks 1 to 6 | Weeks 7 to 9 | Weeks 10 to 12
1 piece every 1 to 2 hours | 1 piece every 2 to 4 hours | 1 piece every 4 to 8 hours

- nicotine gum is a medicine and must be used a certain way to get the best results
- chew the gum slowly until it tingles. Then park it between your cheek and gum. When the tingle is gone, begin chewing again, until the tingle returns.
- repeat this process until most of the tingle is gone (about 30 minutes)
- do not eat or drink for 15 minutes before chewing the nicotine gum, or while chewing a piece
- to improve your chances of quitting, use at least 9 pieces per day for the first 6 weeks
- if you experience strong or frequent cravings, you may use a second piece within the hour. However, do not continuously use one piece after another since this may cause you hiccups, heartburn, nausea or other side effects.
- do not use more than 24 pieces a day
- it is important to complete treatment. If you feel you need to use the gum for a longer period to keep from smoking, talk to your health care provider.

Directions (4 mg)

- if you are under 18 years of age, ask a doctor before use
- before using this product, read the enclosed User’s Guide for complete directions and other important information
- begin using the gum on your quit day
- if you smoke your first cigarette more than 30 minutes after waking up,use 2 mg nicotine gum
- if you smoke your first cigarette within 30 minutes of waking up,use 4 mg nicotine gum according to the following 12 week schedule:

Weeks 1 to 6 | Weeks 7 to 9 | Weeks 10 to 12
1 piece every 1 to 2 hours | 1 piece every 2 to 4 hours | 1 piece every 4 to 8 hours

- nicotine gum is a medicine and must be used a certain way to get the best results
- chew the gum slowly until it tingles. Then park it between your cheek and gum. When the tingle is gone, begin chewing again, until the tingle returns.
- repeat this process until most of the tingle is gone (about 30 minutes)
- do not eat or drink for 15 minutes before chewing the nicotine gum, or while chewing a piece
- to improve your chances of quitting, use at least 9 pieces per day for the first 6 weeks
- if you experience strong or frequent cravings, you may use a second piece within the hour. However, do not continuously use one piece after another since this may cause you hiccups, heartburn, nausea or other side effects.
- do not use more than 24 pieces a day
- it is important to complete treatment. If you feel you need to use the gum for a longer period to keep from smoking, talk to your health care provider

Other information (White Ice Mint)

- (2 mg) each piece contains:calcium 94 mg, sodium 11 mg
- (4 mg) each piece contains:calcium 94 mg, sodium 13 mg
- store at 20 - 25oC (68 - 77oF)
- protect from light

Other information (Original)

- each piece contains:calcium 117 mg, sodium 13 mg
- store at 20 - 25oC (68 - 77oF)
- protect from light

Other information (Cinnamon Surge)

- (2 mg) each piece contains:calcium 94 mg, sodium 11 mg
- (4 mg) each piece contains:calcium 94 mg, sodium 13 mg
- store at 20 - 25oC (68 - 77oF)
- protect from light

Other information (Mint)

- (2 mg) each piece contains:calcium 94 mg, sodium 13 mg
- (4 mg) each piece contains:calcium 94 mg, sodium 14 mg
- store at 20 - 25oC (68 - 77oF)
- protect from light

Other information (Spearmint Burst)

- (2 mg) each piece contains:calcium 94 mg, sodium 11 mg
- (4 mg) each piece contains:calcium 94 mg, sodium 13 mg
- store at 20 - 25oC (68 - 77oF)
- protect from light

Inactive ingredients (White Ice Mint)

each 2 mg piece contains:acesulfame potassium, carnauba wax, edible ink, flavor, gum base, hypromellose, magnesium oxide, menthol, peppermint oil, polysorbate 80, sodium bicarbonate, sodium carbonate, starch, sucralose, titanium dioxide, xylitol

each 4 mg piece contains:acesulfame potassium, carnauba wax, D&C yellow #10 Al. lake, edible ink, flavor, gum base, hypromellose, magnesium oxide, menthol, peppermint oil, polysorbate 80, sodium carbonate, starch, sucralose, titanium dioxide, xylitol

Inactive ingredients (Original)

each 2 mg piece contains:flavors, glycerin, gum base, sodium bicarbonate, sodium carbonate, sorbitol

each 4 mg piece contains:D&C yellow #10, flavors, glycerin, gum base, sodium carbonate, sorbitol

Inactive ingredients (Cinnamon Surge)

each 2 mg piece contains:acacia, acesulfame potassium, carnauba wax, edible ink, gum base, hypromellose, magnesium oxide, menthol, natural and artificial cinnamon flavors, peppermint oil, polysorbate 80, sodium bicarbonate, sodium carbonate, sucralose, titanium dioxide, xylitol

each 4 mg piece contains:acacia, acesulfame potassium, carnauba wax, D&C yellow #10 Al. lake, edible ink, gum base, hypromellose, magnesium oxide, menthol, natural and artificial cinnamon flavors, peppermint oil, polysorbate 80, sodium carbonate, sucralose, titanium dioxide, xylitol

Inactive ingredients (Mint)

each 2 mg piece contains:acesulfame potassium, gum base, magnesium oxide, menthol, peppermint oil, sodium bicarbonate, sodium carbonate, xylitol

each 4 mg piece contains:acesulfame potassium, D&C yellow #10 Al. lake, gum base, magnesium oxide, menthol, peppermint oil, sodium carbonate, xylitol

Inactive ingredients (Spearmint Burst)

each 2 mg piece contains:acacia, acesulfame potassium, carnauba wax, edible ink, flavors, gum base, hypromellose, magnesium oxide, menthol, peppermint oil, polysorbate 80, sodium bicarbonate, sodium carbonate, sucralose, titanium dioxide, xylitol

each 4 mg piece contains:acacia, acesulfame potassium, carnauba wax, D&C yellow #10 Al. lake, edible ink, flavors, gum base, hypromellose, magnesium oxide, menthol, peppermint oil, polysorbate 80, sodium carbonate, sucralose, titanium dioxide, xylitol

Questions or comments?

call toll-free 1-888-569-1743

Additional information found on packaging

Includes Quit Support Program

TO INCREASE YOUR SUCCESS IN QUITTING:

1. You must be motivated to quit.
2. Use Enough– Chew at least 9 piecesof Nicorette gum per day during the first six weeks.
3. Use Long Enough– Use Nicorette gum for the full 12 weeks.
4. Use with a support programas directed in the enclosed User’s Guide.

To remove the gum, tear off single unit.

Peel off backing, starting at corner with loose edge.

Push gum through foil.

- not for sale to those under 18 years of age
- proof of age required
- not for sale in vending machines or from any source where proof of age cannot be verified

This product is protected in sealed blisters. Do not use if individual blisters or printed backings are broken, open, or torn.

Nicorette is proud to offer a free individualized quit support program! Visit www.quit.com/join-myquit for details.

Principal Display Panel

NDC 0135-0474-02 HALEON

NICORETTE

nicotine polacrilex gum, 2 mg stop smoking aid

Gum

2 mg

FOR THOSE WHO SMOKE THEIR FIRST CIGARETTE MORE THAN 30 MINUTES AFTER WAKING UP.

If you smoke your first cigarette WITHIN30 MINUTES of waking up, use Nicorette 4 mg Gum

COATED FOR BOLD FLAVOR

100 PIECES,2 mg EACH

White Ice Mint

824747 Front Label

Principal Display Panel

NDC 0135-0475-02 HALEON

NICORETTE

nicotine polacrilex gum, 4 mg stop smoking aid

Gum

4 mg

FOR THOSE WHO SMOKE THEIR FIRST CIGARETTE WITHIN 30 MINUTES OF WAKING UP.

If you smoke your first cigarette MORE THAN30 MINUTES after waking up, use Nicorette 2 mg Gum.

COATED FOR BOLD FLAVOR

100 PIECES,4 mg EACH

White Ice Mint

824750 Front Label

Principal Display Panel

NDC 0135-0157-11 HALEON

NICORETTE

nicotine polacrilex gum, 2 mg stop smoking aid

Gum

2 mg

FOR THOSE WHO SMOKE THEIR FIRST CIGARETTE MORE THAN 30 MINUTES AFTER WAKING UP.

If you smoke your first cigarette WITHIN30 MINUTES of waking up, use Nicorette 4 mg Gum

200 PIECES,2 mg EACH

Original

824754 Front Label

Principal Display Panel

NDC 0135-0158-11 HALEON

NICORETTE

nicotine polacrilex gum, 4 mg stop smoking aid

Gum

4 mg

FOR THOSE WHO SMOKE THEIR FIRST CIGARETTE WITHIN 30 MINUTES OF WAKING UP.

If you smoke your first cigarette MORE THAN30 MINUTES after waking up, use Nicorette 2 mg Gum.

200 PIECES, 4 mg EACH

Original

824757 Front Label

Principal Display Panel

NDC 0135-0466-02 HALEON

NICORETTE

nicotine polacrilex gum, 2 mg stop smoking aid

Gum

2 mg

FOR THOSE WHO SMOKE THEIR FIRST CIGARETTE MORE THAN 30 MINUTES AFTER WAKING UP.

If you smoke your first cigarette WITHIN30 MINUTES of waking up, use Nicorette 4 mg Gum

COATED FOR BOLD FLAVOR

100 PIECES

2 mg EACH

Cinnamon Surge

824735 Front Label

Principal Display Panel

NDC 0135-0467-02 HALEON

NICORETTE

nicotine polacrilex gum, 4 mg stop smoking aid

Gum

4 mg

FOR THOSE WHO SMOKE THEIR FIRST CIGARETTE WITHIN 30 MINUTES OF WAKING UP.

If you smoke your first cigarette MORE THAN30 MINUTES after waking up, use Nicorette 2 mg Gum.

COATED FOR BOLD FLAVOR

100 PIECES

4 mg EACH

Cinnamon Surge

824738 Front Label

Principal Display Panel

NDC 0135-0229-05 HALEON

NICORETTE

nicotine polacrilex gum, 2 mg stop smoking aid

Gum

2 mg

FOR THOSE WHO SMOKE THEIR FIRST CIGARETTE MORE THAN 30 MINUTES AFTER WAKING UP.

If you smoke your first cigarette WITHIN30 MINUTES of waking up, use Nicorette 4 mg Gum

170 PIECES, 2 mg EACH

Mint

824762 Front Label

Principal Display Panel

NDC 0135-0230-05 HALEON

NICORETTE

nicotine polacrilex gum, 4 mg stop smoking aid

Gum

4 mg

FOR THOSE WHO SMOKE THEIR FIRST CIGARETTE WITHIN 30 MINUTES OF WAKING UP.

If you smoke your first cigarette MORE THAN30 MINUTES after waking up, use Nicorette 2 mg Gum

170 PIECES, 4 mg EACH

Mint

824763 Front Label

Principal Display Panel

NDC 0135-0532-02 HALEON

NICORETTE

nicotine polacrilex gum, 2 mg stop smoking aid

Gum

2 mg

FOR THOSE WHO SMOKE THEIR FIRST CIGARETTE MORE THAN 30 MINUTES AFTER WAKING UP.

If you smoke your first cigarette WITHIN30 MINUTES of waking up, use Nicorette 4 mg Gum

COATED FOR BOLD FLAVOR

100 PIECES, 2 mg EACH

Spearmint Burstwith a hint of chamomile

824758 Front Label

Principal Display Panel

NDC 0135-0533-02 HALEON

NICORETTE

nicotine polacrilex gum, 2 mg stop smoking aid

Gum

4 mg

FOR THOSE WHO SMOKE THEIR FIRST CIGARETTE MORE THAN 30 MINUTES AFTER WAKING UP.

If you smoke your first cigarette WITHIN30 MINUTES of waking up, use Nicorette 2 mg Gum

COATED FOR BOLD FLAVOR

100 PIECES, 4 mg EACH

Spearmint Burstwith a hint of chamomile

824760 Front Label

Principal Display Panel

NDC 0135-0355-03 HALEON

NICORETTE

nicotine polacrilex gum, 4 mg stop smoking aid

Gum

4 mg

FOR THOSE WHO SMOKE THEIR FIRST CIGARETTE WITHIN 30 MINUTES OF WAKING UP.

If you smoke your first cigarette MORE THAN30 MINUTES after waking up, use Nicorette 2 mg Gum

COATED FOR BOLD FLAVOR

160 PIECES, 4 mg EACH

Spearmint Burstwith a hint of chamomile

824761 Front Label